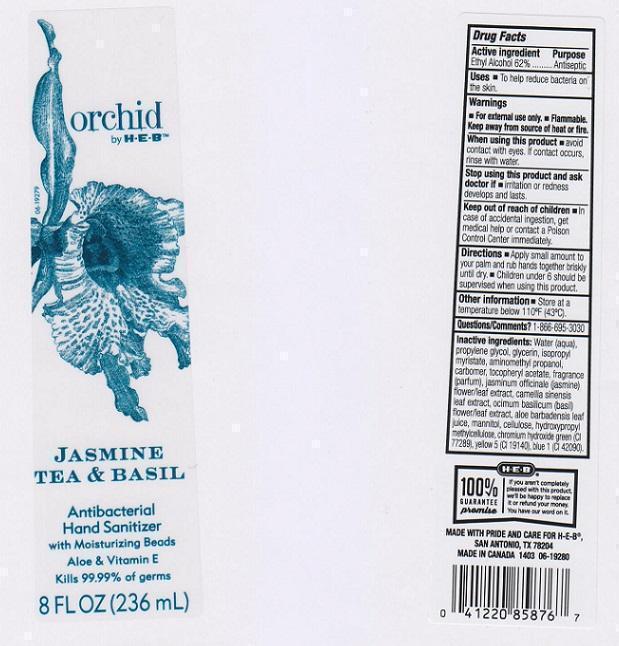 DRUG LABEL: ORCHID
NDC: 37808-066 | Form: LIQUID
Manufacturer: H E B
Category: otc | Type: HUMAN OTC DRUG LABEL
Date: 20150116

ACTIVE INGREDIENTS: ALCOHOL 620 mg/1 mL
INACTIVE INGREDIENTS: WATER; PROPYLENE GLYCOL; GLYCERIN; ISOPROPYL MYRISTATE; AMINOMETHYLPROPANOL; CARBOMER 934; .ALPHA.-TOCOPHEROL ACETATE; JASMINUM OFFICINALE FLOWER; GREEN TEA LEAF; OCIMUM BASILICUM FLOWERING TOP; ALOE VERA LEAF; MANNITOL; POWDERED CELLULOSE; HYPROMELLOSES; CHROMIUM HYDROXIDE GREEN; FD&C YELLOW NO. 5; FD&C BLUE NO. 1

DRUG FACTS

ACTIVE INGREDIENT

ETHYL ALCOHOL 62%

PURPOSE

ANTISEPTIC

USES

TO HELP REDUCE BACTERIA ON THE SKIN

WARNINGS

- FOR EXTERNAL USE ONLY
- FLAMMABLE
- KEEP AWAY FROM SOURCE OF HEAT OR FIRE

WHEN USING THIS PRODUCT

AVOID CONTACT WITH EYES. IF CONTACT OCCURS, RINSE WITH WATER

STOP USING THIS PRODUCT AND ASK DOCTOR IF

IRRITATION OR REDNESS DEVELOPS AND LASTS

KEEP OUT OF REACH OF CHILDREN

IN CASE OF ACCIDENTAL INGESTION, GET MEDICAL HELP OR CONTACT A POISON CONTROL CENTER IMMEDIATELY

DIRECTIONS

- APPLY SMALL AMOUNT TO YOUR PALM AND RUB HANDS TOGETHER BRISKLY UNTIL DRY
- CHILDREN UNDER 6 SHOULD BE SUPERVISED WHEN USING THIS PRODUCT

OTHER INFORMATION

STORE AT A TEMPERATURE BELOW 110°F (43°C)

INACTIVE INGREDIENTS

WATER (AQUA), PROPYLENE GLYCOL, GLYCERIN, ISOPROPYL MYRISTATE, AMINOMETHYL PROPANOL, CARBOMER, TOCOPHERYL ACETATE, FRAGRANCE (PARFUM), JASMINUM OFFICINALE (JASMINE) FLOWER/LEAF EXTRACT, CAMELLIA SINENSIS LEAF EXTRACT, OCIMUM BASILICUM (BASIL) FLOWER/LEAF, ALOE BARBADENSIS LEAF JUICE, MANNITOL, CELLULOSE, HYDROXYPROPYL METHYLCELLULOSE, CHROMIUM HYDROXIDE GREEN (CI 77289), YELLOW 5 (CI 19140), BLUE 1 (CI 42090)